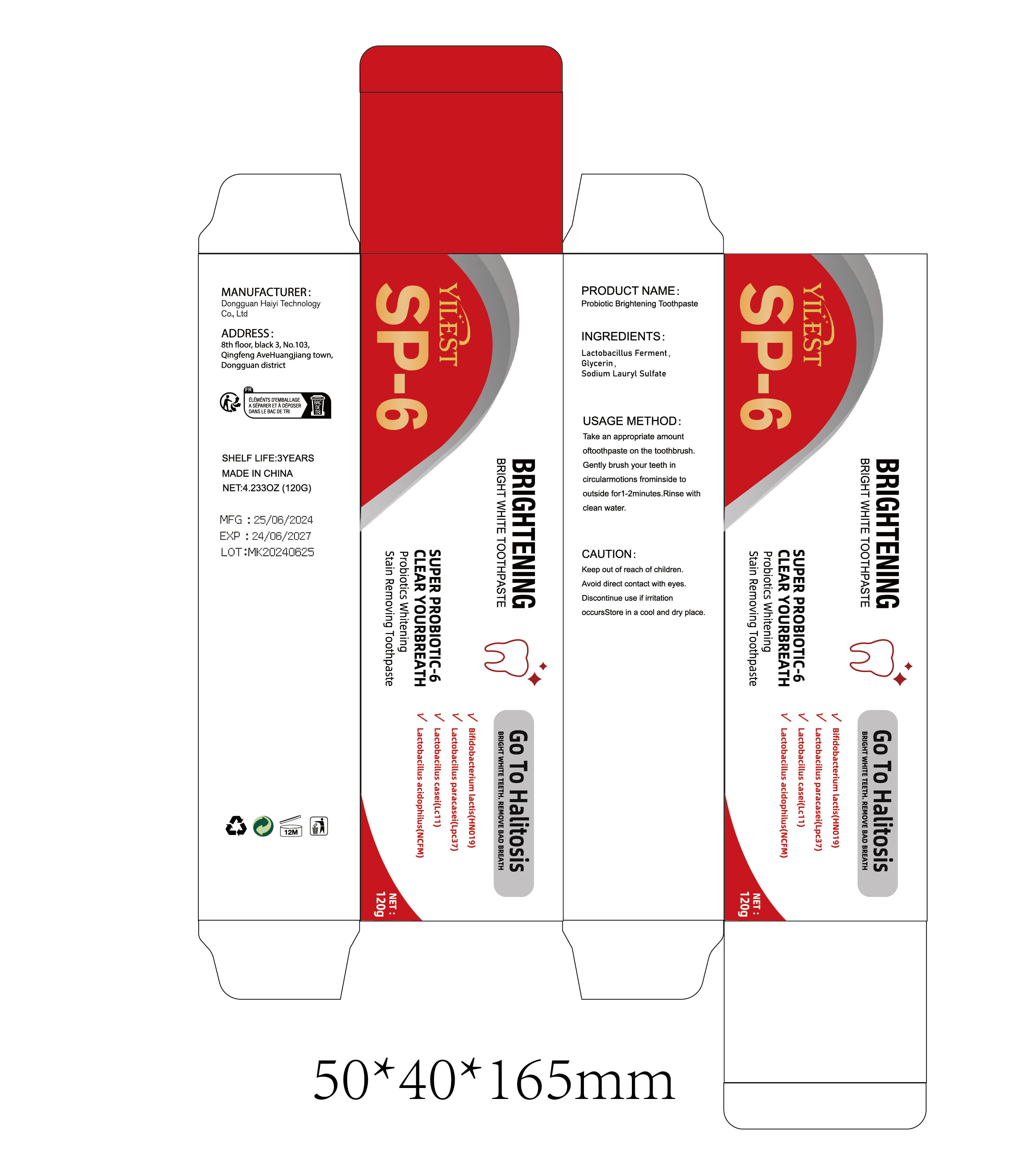 DRUG LABEL: Probiotic Brightening
NDC: 84732-020 | Form: PASTE
Manufacturer: Dongguan Haiyi Technology Co.,Ltd.
Category: otc | Type: HUMAN OTC DRUG LABEL
Date: 20240927

ACTIVE INGREDIENTS: LIMOSILACTOBACILLUS FERMENTUM 1 g/120 g
INACTIVE INGREDIENTS: GLYCERIN; SODIUM LAURYL SULFATE

Active ingredient

Lactobacillus Ferment

Inactive ingredient

Glycerin ,Sodium Lauryl Sulfate

Purpose section

Go To Halitosis；

BRIGHT WHITE TEETH；

REMOVE BAD BREATH；

Warning

Keep out of reach of children.
Avoid direct contact with eyes.
Discontinue use if irritationoccurs

Store in a cool and dry place.

stop use

This product may cause allergic reactions in asmall number of people.
lf youexperience any discomfort,please stop using it immediately.

not use

Not suitable for use by children, pregnantor breastfeeding people.

OUT OF CHILDREN

KEEP THE PRODUCT OUT OF REACH OF CHILDREN to

HOW TO USE

Take an appropriate amount oftoothpaste on the toothbrush.Gently brush your teeth in circularmotions frominside to outside for 1-2 minutes.Rinse with clean water.

Dosage

Give it twice a day, once in the morning and evening